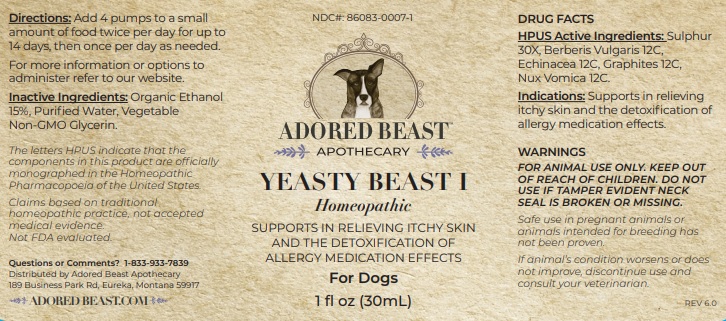 DRUG LABEL: YEASTY BEAST I
NDC: 86083-0007 | Form: LIQUID
Manufacturer: The Adored Beast Apothecary, Ltd
Category: homeopathic | Type: OTC ANIMAL DRUG LABEL
Date: 20251027

ACTIVE INGREDIENTS: SULFUR 30 [hp_X]/30 mL; BERBERIS VULGARIS ROOT BARK 12 [hp_C]/30 mL; ECHINACEA, UNSPECIFIED 12 [hp_C]/30 mL; GRAPHITE 12 [hp_C]/30 mL; STRYCHNOS NUX-VOMICA SEED 12 [hp_C]/30 mL
INACTIVE INGREDIENTS: ALCOHOL; WATER; GLYCERIN

YEASTY BEAST I

DRUG FACTS
HPUS Active Ingredients:

Sulphur 30X, Berberis Vulgaris 12C, Echinacea 12C, Graphites 12C, Nux Vomica 12C.

The letters HPUS indicate that the components in this product are officially monographed in the Homeopathic Pharmacopoeia of the United States.
Claims based on traditional homeopathic practice, not accepted medical evidence. Not FDA evaluated.

INDICATIONS AND USAGE

Indications: Supports in relieving itchy skin and the detoxification of allergy medication effects.

WARNINGS
FOR ANIMAL USE ONLY. KEEP OUT
OF REACH OF CHILDREN. DO NOT
USE IF TAMPER EVIDENT NECK
SEAL IS BROKEN OR MISSING.

KEEP OUT OF REACH OF CHILDREN.

DOSAGE AND ADMINISTRATION

Directions: Add 4 pumps to a small amount of food twice per day for up to 14 days, then once per day as needed.
For more information or options to administer refer to our website.

INACTIVE INGREDIENT

Inactive Ingredients: Organic Ethanol 15%, Purified Water, Vegetable Non-GMO Glycerin.

Questions or Comments? 1-833-933-7839

Distributed by Adored Beast Apothecary

189 Business Park Rd, Eureka, Montana 59917

PACKAGE LABEL

ADORED BEAST

APOTHECARY

YEASTY BEAST I

Homeopathic

SUPPORTS IN RELIEVING ITCHY SKIN

AND THE DETOXIFICATION OF ALLERGY MEDICATION EFFECTS

For Dogs

1 fl oz (30mL)

PURPOSE

Supports in relieving itchy skin and the detoxification of allergy medication effects.